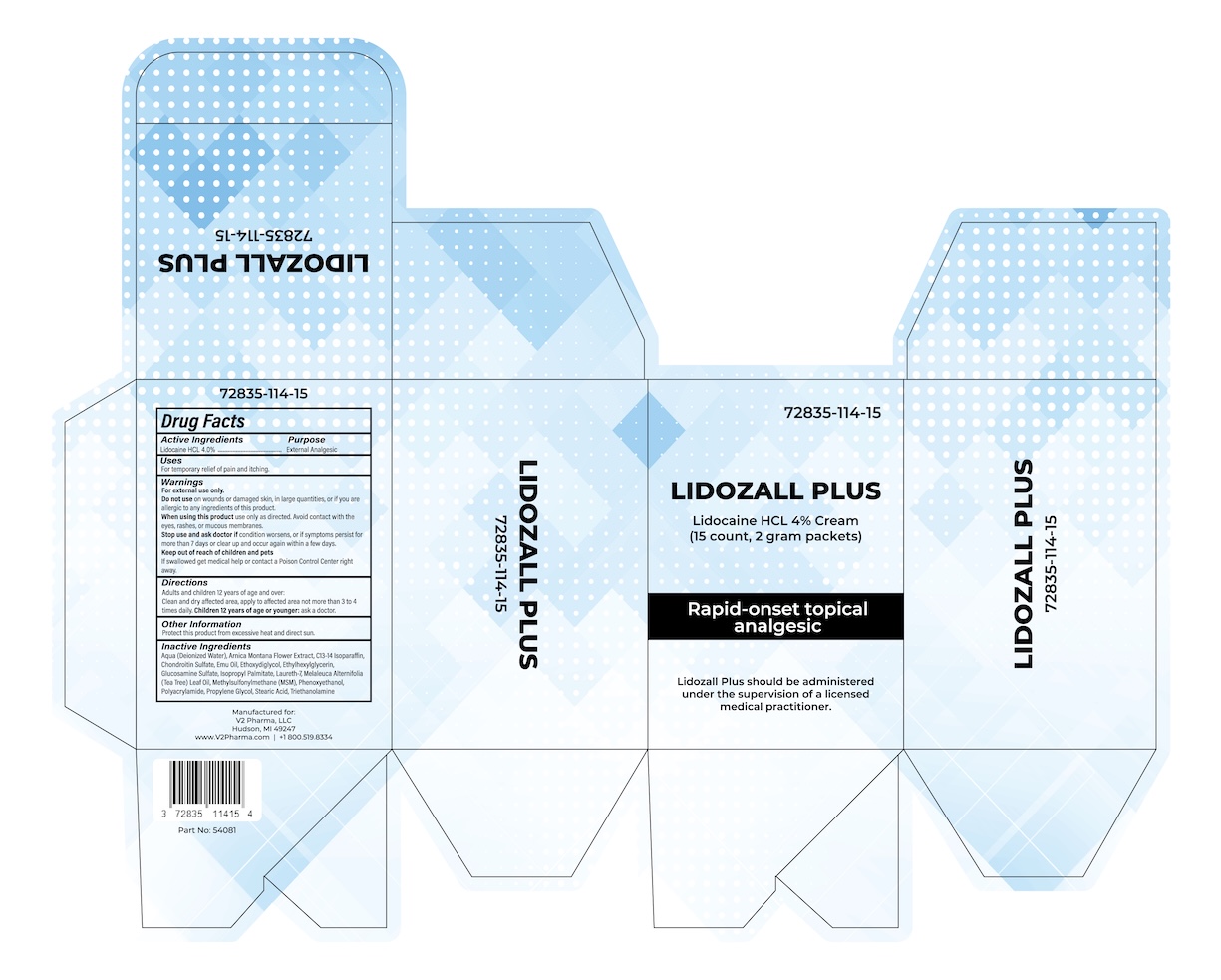 DRUG LABEL: Lidozall Plus
NDC: 72835-114 | Form: CREAM
Manufacturer: V2 Pharma LLC
Category: otc | Type: HUMAN OTC DRUG LABEL
Date: 20251112

ACTIVE INGREDIENTS: LIDOCAINE HYDROCHLORIDE 4 g/100 g
INACTIVE INGREDIENTS: ARNICA MONTANA FLOWER; WATER; C13-14 ISOPARAFFIN; SODIUM CHONDROITIN SULFATE (PORCINE; 5500 MW); EMU OIL; DIETHYLENE GLYCOL MONOETHYL ETHER; ETHYLHEXYLGLYCERIN; GLUCOSAMINE SULFATE; ISOPROPYL PALMITATE; MELALEUCA ALTERNIFOLIA LEAF; DIMETHYL SULFONE; PHENOXYETHANOL; PROPYLENE GLYCOL; STEARIC ACID; TROLAMINE

Lidozall Plus

Lidozall Plus

Rapid-onset topical analgesic

Active Ingredients

Lidocaine HCL 4.0% w/w

Purpose

External analgesic

Uses

For temporary relief of pain and itching due to minor skin irritations.

Warnings

- For external use only.
- Avoid contact with eyes.

- Do not use in large quantities, particularly over raw surfaces or blistered areas.

- Stop use and ask a doctor if condition worsens, or if symptoms persist for more than 7 days or clear up and occur again within a few days. Discontinue use.

- Keep out of reach of children. If product is swallowed, get medical help or contact a Poison Control Center right away.

Directions

For adults and children two-years or older: Apply 1 packet (2 grams) topically to the affected area(s) up to 4 times daily as needed for pain. Do not use more than 4 packets (8 grams) per day.

Inactive Ingredients

Aqua (Deionized Water), Arnica Montana Floweri Extract, C13-14 Isoparaffin, Chondroitin Sulfate, Emu Oil, Ethoxydiglycol, Ethylhexylglycerin, Glucosamine Sulfate, Isopropyl Palmitate, Laureth-7, Melaleuca Alternifolia (Tea Tree) Oil, Methylsulfonylmenthane (MSM), Phenoxyethanol, Polyacrylamide, Propylene Glycol, Stearic Acid, Triethanolamine.

Other Information

Protect this product from excessive heat and direct sun.